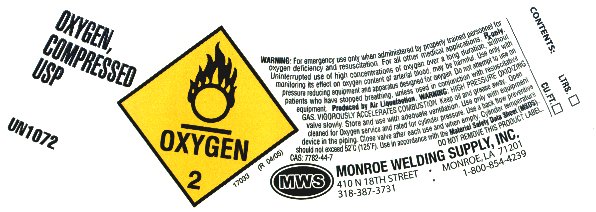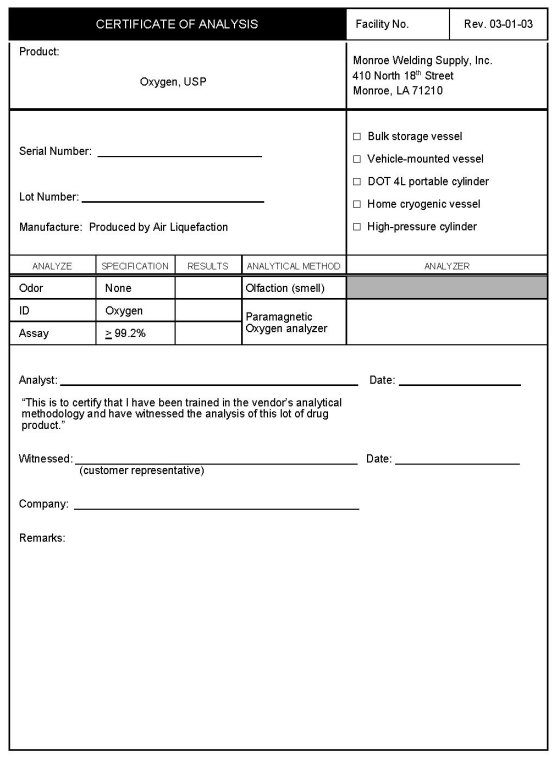 DRUG LABEL: oxygen
NDC: 52233-001 | Form: GAS
Manufacturer: Monroe Welding Supply, Inc.
Category: prescription | Type: HUMAN PRESCRIPTION DRUG LABEL
Date: 20100824

ACTIVE INGREDIENTS: oxygen 992 mL/1 L

Oxygen, compressed

PACKAGE LABEL

OXYGEN, COMPRESSED USP
UN 1072
WARNING: For emergency use only when administered by properly trained personnel for oxygen deficiency and resuscitation. For all other medical applications, Rx only. Uninterrupted use of high concentrations of oxygen over a long duration, without monitoring its effect on oxygen content of arterial blood, may be harmful. Use only with pressure reducing equipment and apparatus designed for oxygen. Do not attempt to use on patients who have stopped breathing, unless used in conjunction with resuscitative equipment. Produced by Air Liquefaction. WARNING: HIGH PRESSURE OXIDIZING GAS. VIGOROUSLY ACCELERATES COMBUSTION. Keep oil and grease away. Open valve slowly. Store and use with adequate ventilation. Use only with equipment cleaned for Oxygen service and rated for cylinder pressure. Use a backflow preventive device in the piping. Close valve after each use and when empty. Cylinder temperature should not exceed 52oC (125oF). Use in accordance with the Material Safety Data Sheet (MSDS).
CAS:7782-44-7
DO NOT REMOVE THIS PRODUCT LABEL
17033 (R 04/05)
MONROE WELDING SUPPLY, INC.
410 N 18TH STREET MONROE, LA 71201
318-387-3731 1-800-854-4239
CONTENTS: LTRS.______ CU.FT. ______

Oxygen, certificate of analysis

CERTIFICATE OF ANALYSIS Facility No. Rev. 03-01-03
Product: Oxygen, USP Monroe Welding Supply, Inc. 410 North 18th Street Monroe, LA 71210
Serial No.__________
Lot No. __________
Manufacture: Produced by Air Liquefaction
Bulk storage vessel Vehicle-mounted vessel DOT 4L portable cylinder Home cryogenic vessel High-pressure cylinder
ANALYZE SPECIFICATION RESULTS ANALYTICAL METHOD ANALYZER
Odor None _____ Olfaction (smell)
ID Oxygen _____ Paramagnetic Oxygen analyzer
Assay >99.2 _____
Analyst __________ Date:_____
“This is to certify that I have been trained in the vendor’s analytical methodology and have witnessed the analysis of this lot of drug product”
Witnessed: __________ (Customer representative) Date: _____
Company:__________
Remarks: